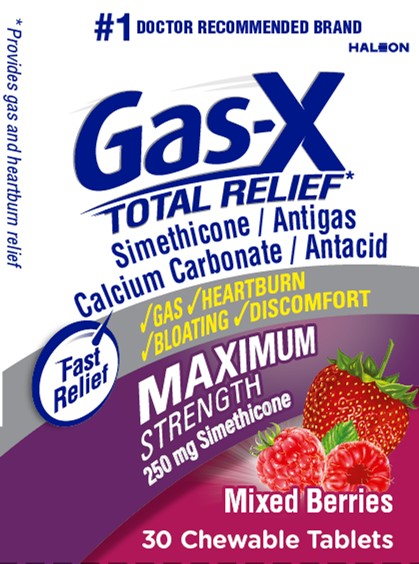 DRUG LABEL: Gas-X

NDC: 0067-0118 | Form: TABLET, CHEWABLE
Manufacturer: Haleon US Holdings LLC
Category: otc | Type: HUMAN OTC DRUG LABEL
Date: 20250715

ACTIVE INGREDIENTS: CALCIUM CARBONATE 750 mg/1 1; DIMETHICONE, UNSPECIFIED 250 mg/1 1
INACTIVE INGREDIENTS: ACACIA; YELLOW WAX; CARNAUBA WAX; ANHYDROUS CITRIC ACID; STARCH, CORN; CORN SYRUP; DEXTRIN PALMITATE (CORN; 20000 MW); FD&C BLUE NO. 2 ALUMINUM LAKE; FD&C RED NO. 40; FD&C RED NO. 40 ALUMINUM LAKE; FD&C YELLOW NO. 5 ALUMINUM LAKE; MALTODEXTRIN; MEDIUM-CHAIN TRIGLYCERIDES; METHYLPARABEN; BUTYL ALCOHOL; PHOSPHORIC ACID; PROPYLENE GLYCOL; PROPYLPARABEN; WATER; SHELLAC; SODIUM BENZOATE; SORBIC ACID; SORBITOL; SOYBEAN LECITHIN; SUCROSE; TITANIUM DIOXIDE; CORN OIL

Drug Facts

Active ingredients (per tablet)

Calcium carbonate 750 mg

Simethicone 250 mg

Purposes

Antacid

Antigas

Uses

for the relief of

- pressure, bloating, and fullness commonly referred to as gas
- gas associated with heartburn, sour stomach or acid indigestion
- acid indigestion
- heartburn
- sour stomach
- upset stomach associated with these symptoms

Warnings

Ask a doctor or pharmacist before use if you are

presently taking a prescription drug. Antacids may interact with certain prescription drugs.

When using this product

- do not exceed 2 tablets in 24 hours except under the advice and supervision of a doctor
- do not use the maximum dosage for more than 2 weeks, except under the advice and supervision of a doctor

Directions

- adults and children 12 years and older:chew 1 or 2 tablets as symptoms occur, or as directed by a doctor. Chew or crush tablets completely before swallowing.
- do not take for symptoms that persist for more than 2 weeks unless advised by a doctor

Other information

- each tablet contains:elemental calcium 300 mg
- do not store above 25°C (77°F)
- contains FD&C Yellow No. 5 (tartrazine) as a color additive

Inactive ingredients

acacia, beeswax, carmine, carnauba wax, citric acid, corn starch, corn syrup, dextrin, FD&C blue no.2 aluminum, FD&C red no. 40, FD&C red no. 40 aluminum lake, FD&C yellow no. 5 aluminum lake (tartrazine), maltodextrin, medium chain triglycerides, methylparaben, natural and artificial flavors, pharmaceutical ink, phosphoric acid, propylene glycol, propylparaben, purified water, shellac,
sodium benzoate, sorbic acid, sorbitol, soy lecithin, sucrose, titanium dioxide, vegetable oil

Questions or comments?

1-800-452-0051

Additional Information

Do not use if printed inner safety seal under cap is broken or missing.

Principal Display Panel

#1 DOCTOR RECOMMENDED BRAND

HALEON

Gas-X

TOTAL RELIEF*

Simethicone / Antigas

Calcium Carbonate / Antacid

*Provides gas and heartburn relief

Fast Relief

√ GAS √ HEARTBURN √ BLOATING √ DISCOMFORT

MAXIMUM

STRENGTH

250 mg Simethicone

Mixed Berries

30 Chewable Tablets

218342 – Front Label